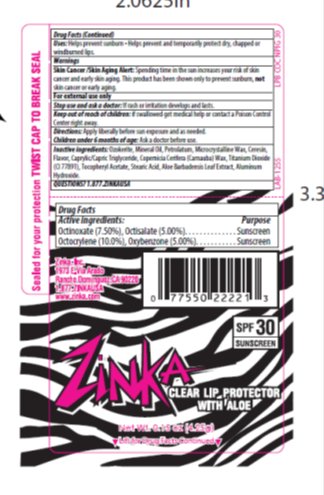 DRUG LABEL: Zinka Lip Protector SPF 30 Lip Balm
NDC: 52993-125 | Form: STICK
Manufacturer: Zinka
Category: otc | Type: HUMAN OTC DRUG LABEL
Date: 20140821

ACTIVE INGREDIENTS: OCTINOXATE 7.5 mg/1 g; OXYBENZONE 5.0 mg/1 g; OCTOCRYLENE 10 mg/1 g; OCTISALATE 5 mg/1 g
INACTIVE INGREDIENTS: PETROLATUM 10 mg/1 g; LIGHT MINERAL OIL 23.75 mg/1 g; MICROCRYSTALLINE WAX 4.00 mg/1 g; CERESIN 27 mg/1 g

Drug Facts

Active ingredient

Octinoxate (7.5%), Oxybenzone (5.0%), Octisalate (5.0%), Octocrylene (10.0%)

Purpose

Sunscreen

Keep Out of Reach of Children

If swallowed get medical help or contact a Poison Control Center right away.

Uses

Helps prevent sunburn. Helps prevent and temporarily protects dry, chapped or windburned lips.

Warnings

Skin Cancer/Skin Aging Alert: Spending time in the sun increases your risk of skin cancer and early skin aging. This product has been shown only to prevent sunburn, not skin cancer or early aging.

For external use only: Stop use and ask a doctor: if rash or irritation develops and lasts.

Directions

Apply liberally before sun exposure and as needed. Children under 6 months of age: Ask a doctor before use.

Inactive Ingredients

Ozokerite, Mineral Oil, Petrolatum, Microcrystalline Wax, Ceresin, Flavor, Caprylic/Capric Triglyceride, Copernicia Cerifera (Carnauba) Wax, Titanium Dioxide (CI 77891), Tocopheryl Acetate, Stearic Acid, Aloe Barbadenis Leaf Extract, Aluminum Hydroxide.